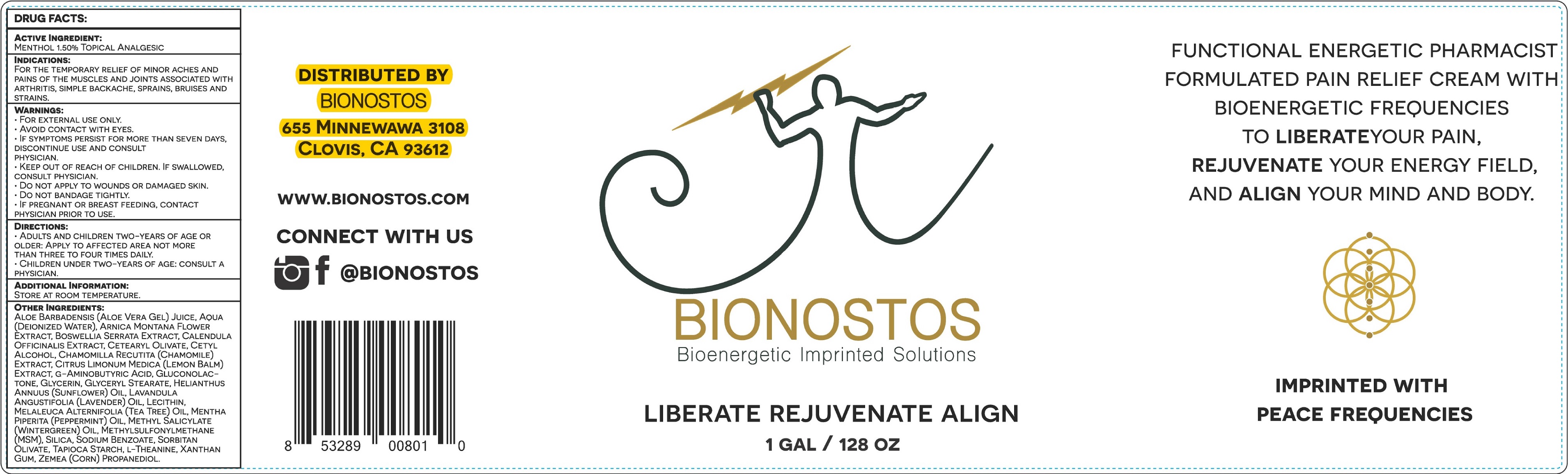 DRUG LABEL: MIND BODY MATRIX PAIN RELIEF
NDC: 72268-175 | Form: CREAM
Manufacturer: Functional Energetic, Inc.
Category: otc | Type: HUMAN OTC DRUG LABEL
Date: 20240125

ACTIVE INGREDIENTS: MENTHOL 15 mg/1 mL
INACTIVE INGREDIENTS: ALOE VERA LEAF; WATER; ARNICA MONTANA FLOWER; INDIAN FRANKINCENSE; CALENDULA OFFICINALIS FLOWER; CETEARYL OLIVATE; CETYL ALCOHOL; CHAMOMILE; GLUCONOLACTONE; GLYCERIN; GLYCERYL STEARATE CITRATE; HELIANTHUS ANNUUS FLOWERING TOP; LAVENDER OIL; MELALEUCA ALTERNIFOLIA LEAF; PEPPERMINT OIL; METHYL SALICYLATE; DIMETHYL SULFONE; SILICON DIOXIDE; SODIUM BENZOATE; SORBITAN OLIVATE; STARCH, TAPIOCA; THEANINE; XANTHAN GUM; CORN

MIND-BODY MATRIX PAIN RELIEF CREAM

ACTIVE INGREDIENT:

MENTHOL 1.50%

PURPOSE

TOPICAL ANALGESIC

INDICATIONS:

FOR THE TEMPORARY RELIEF OF MINOR ACHES AND PAINS OF THE MUSCLES AND JOINTS ASSOCIATED WITH ARTHRITIS, SIMPLE BACKACHE, SPRAINS, BRUISES AND STRAINS.

WARNINGS:

- FOR EXTERNAL USE ONLY.
- AVOID CONTACT WITH EYES.
- IF SYMPTOMS PERSIST FOR MORE THAN SEVEN DAYS, DISCONTINUE USE AND CONSULT PHYSICIAN.

KEEP OUT OF REACH OF CHILDREN.

IF SWALLOWED, CONSULT PHYSICIAN

DO NOT APPLY

- TO WOUNDS OR DAMAGED SKIN.
- DO NOT BANDAGE TIGHTLY.

IF PREGNANT OR BREAST FEEDING,

CONTACT PHYSICIAN PRIOR TO USE.

DIRECTIONS:

- ADULTS AND CHILDREN TWO-YEARS OF AGE OR OLDER: APPLY TO AFFECTED AREA NOT MORE THAN THREE TO FOUR TIMES DAILY.
- CHILDREN UNDER TWO-YEARS OF AGE: CONSULT A PHYSICIAN.

ADDITIONAL INFORMATION:

STORE AT ROOM TEMPERATURE.

OTHER INGREDIENTS:

ALOE BARBADENSIS (ALOE VERA GEL) JUICE, AQUA (DEIONIZED WATER), ARNICA MONTANA FLOWER EXTRACT, BOSWELLIA SERRATA EXTRACT, CALENDULA 0FFICINALIS EXTRACT, CETEARYL OLIVATE, CETYL ALCOHOL, CHAMOMILLA RECUTITA (CHAMOMILE) EXTRACT, CITRUS LIMONUM MEDICA (LEMON BALM) EXTRACT, G-AMINOBUTYRIC ACID, GLUCONOLACTONE, GLYCERIN, GLYCERYL STEARATE, HELIANTHUS
ANNUUS (SUNFLOWER) OIL, LAVANDULA ANGUSTIFOLIA (LAVENDER) OIL, LECITHIN, MELALEUCA ALTERNIFOLIA (TEA TREE) OIL, MENTHA
PIPERITA (PEPPERMINT) OIL, METHYL SALICYLATE (WINTERGREEN) OIL, METHYLSULFONYLMETHANE (MSM), SILICA, SODIUM BENZOATE, SORBITAN OLIVATE, TAPIOCA STARCH, L-THEANINE, XANTHAN GUM, ZEMEA (CORN) PROPANEDIOL.